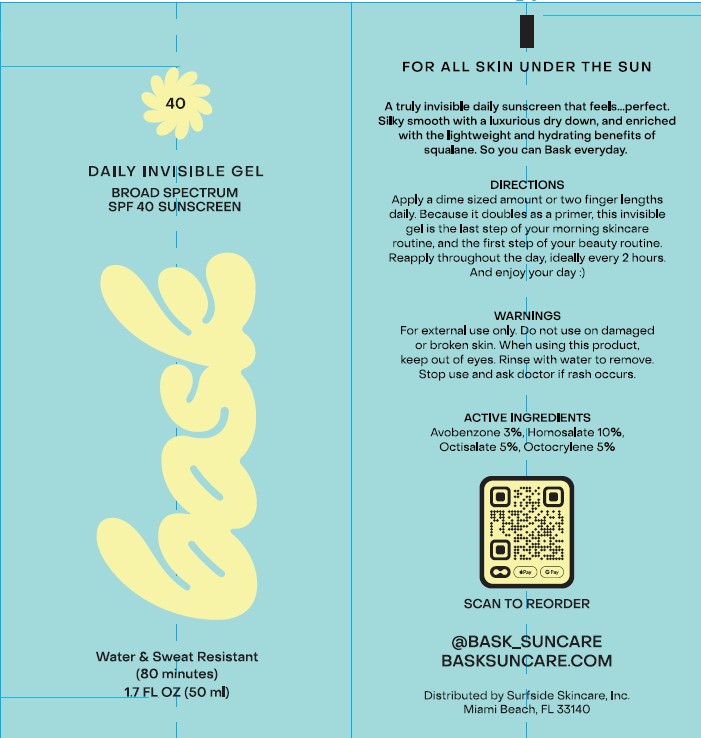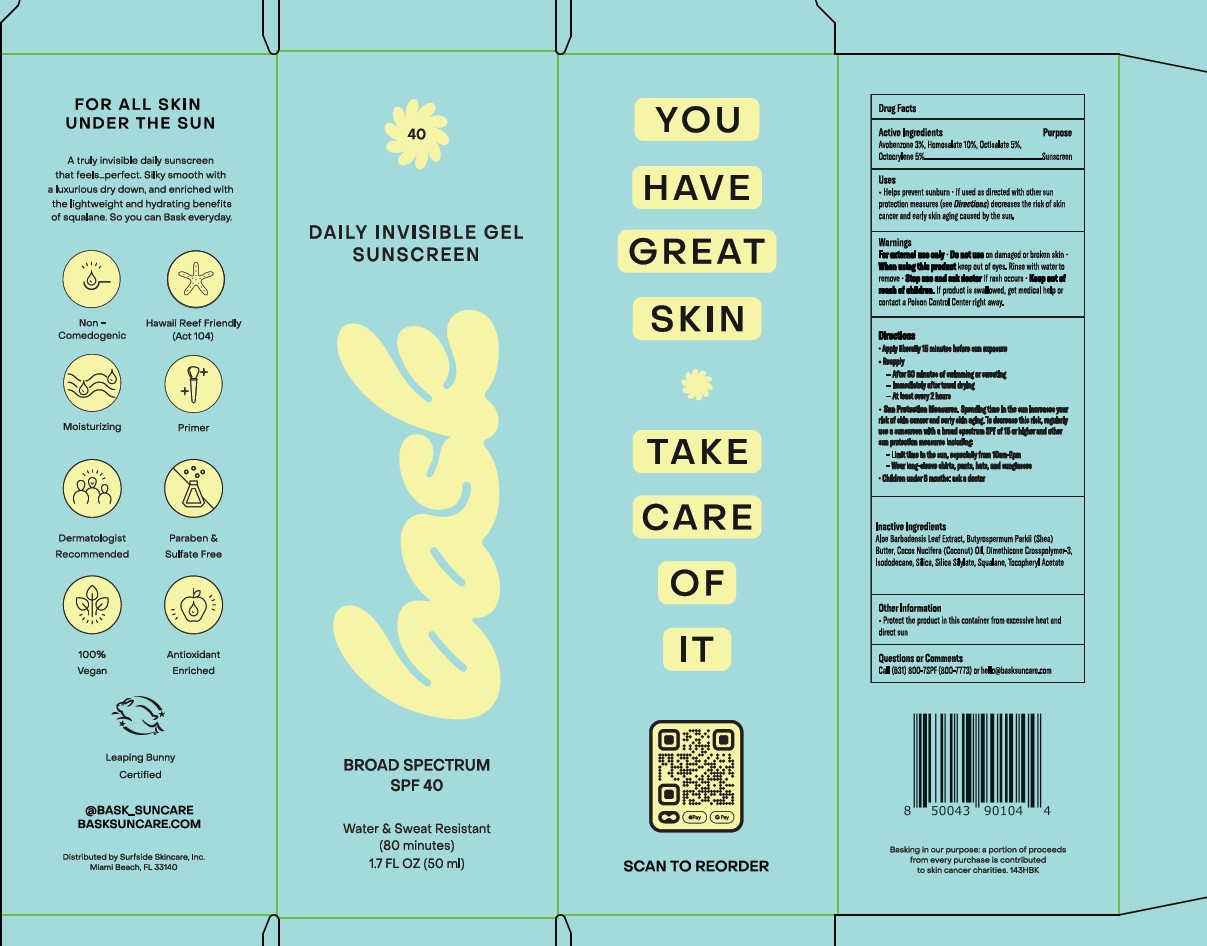 DRUG LABEL: Bask
NDC: 87244-001 | Form: GEL
Manufacturer: Surfside Skincare, Inc. dba Bask Suncare
Category: otc | Type: HUMAN OTC DRUG LABEL
Date: 20260209

ACTIVE INGREDIENTS: OCTISALATE 10 g/100 mL; HOMOSALATE 10 g/100 mL; AVOBENZONE 3 g/100 mL; OCTOCRYLENE 5 g/100 mL
INACTIVE INGREDIENTS: SQUALANE; DIMETHICONE CROSSPOLYMER; ISODODECANE; ALOE VERA LEAF; SHEA BUTTER; .ALPHA.-TOCOPHEROL ACETATE; SILICON DIOXIDE; COCONUT OIL

Bask SPF 40 Invisible Gel (BFGEL231, 22D13-115034-LB062) [as PLD]

Active Ingredients

Avobenzone 3%

Homosalate 10%

Octisalate 5%

Octocrylene 5%

Purpose

Sunscreen

Uses

- helps prevent sunburn
- if used as directed with other sun protection measures (see Directions) decreases the risk of skin cancer and early skin aging caused by the sun

Warnings

For external use only

Do not use

on damaged or broken skin

When using this product

keep out of eyes. Rinse with water to remove.

Stop use and ask doctor

if rash occurs

Keep out of reach of children

If product is swallowed, get medical help or contact a Poison Control Center right away

Directions

- apply liberally 15 minutes before sun exposure
- reapply:
- after 80 minutes of swimming or sweating
- immediately after towel drying
- at least every 2 hours
- Sun Protection Measures. Spending time in the sun increases your risk of skin cancer and early skin aging. To decrease this risk, regularly use a sunscreen with a broad spectrum SPF of 15 or higher and other sun protection measures including:
- Limit time in the sun, especially from 10am - 2pm
- Wear long-sleeve shirts, pants, hats, and sunglasses
- Children under 6 months: ask a doctor

Inactive Ingredients

Aloe Barbadensis Leaf Extract, Butyrospermum Parkii (Shea) Butter, Cocos Nucifera (Coconut) Oil, Dimethicone Crosspolymer-3, Isododecane, Silica, Silica Silylate, Squalane, Tocopheryl Acetate

Other Information

- Protect the product in this container from excessive heat and direct sun

Questions or Comments

Call (631) 800-7SPF (800-7773) or hello@basksuncare.com